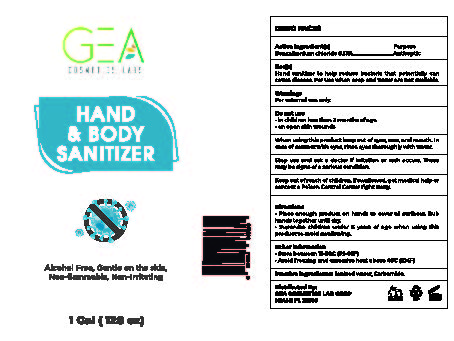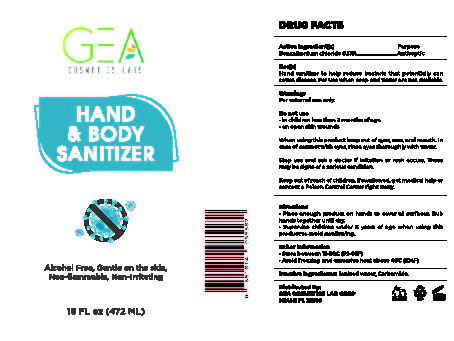 DRUG LABEL: GEA Cosmetics Labs Hand and Body Sanitizer
NDC: 81237-001 | Form: SPRAY
Manufacturer: Romano Group, LLC
Category: otc | Type: HUMAN OTC DRUG LABEL
Date: 20210101

ACTIVE INGREDIENTS: BENZALKONIUM CHLORIDE 0.61 g/472 mL
INACTIVE INGREDIENTS: WATER; UREA

GEA Cosmetics Labs Hand & Body Sanitizer

Active Ingredient

Benzalkonium Chloride 0.13%

Purpose

Antiseptic

Uses

Hand Sanitizer to to help reduce bacteria that potentially can cause disease. For use when soap and water are not available.

Warnings

For External Use only.

Do Not Use

On children less that 2 months of age

on open skin wounds

When using this product

keep out of eyes, ears, and mouth, in case of contact with eyes, rinse eyes thoroughly with water

Keep out of reach of children.

If swallowed, get medical help or contact a Poison Control Center right away

Directions

- Place enough product on hands to cover all surfaces. Rub hands together until dry.
- Supervise children under 6 years of age when using this product to avoid swallowing.

Other Information

Store between 15-30C (59-86F)
Avoid Freezing and excessive heat above 40C (104F)

Inactive Ingredients

Ionized water, Carbamide